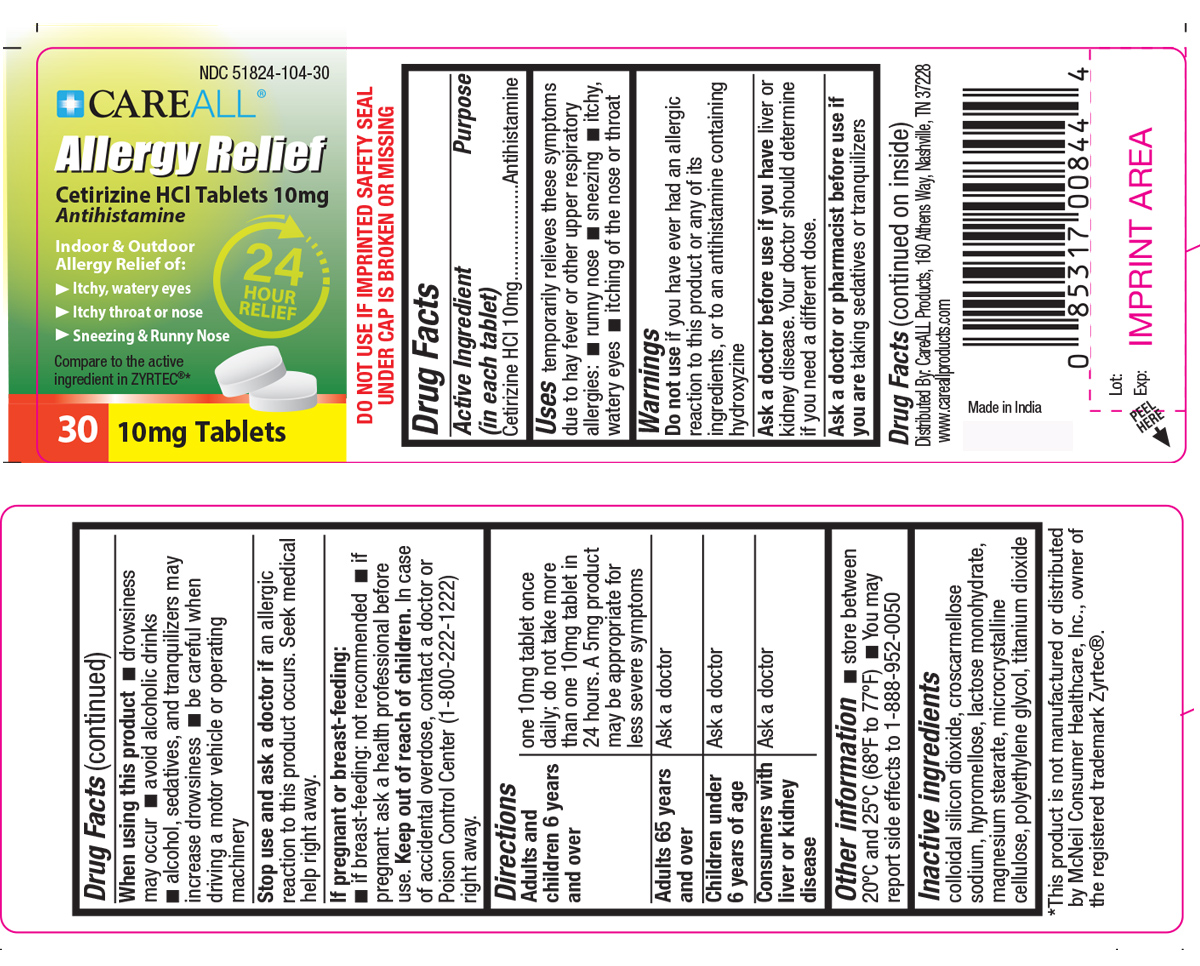 DRUG LABEL: CAREALL Allergy Relief
NDC: 51824-104 | Form: TABLET
Manufacturer: New World Imports
Category: otc | Type: HUMAN OTC DRUG LABEL
Date: 20251201

ACTIVE INGREDIENTS: CETIRIZINE HYDROCHLORIDE 10 mg/1 1
INACTIVE INGREDIENTS: LACTOSE MONOHYDRATE; CROSCARMELLOSE SODIUM; SILICON DIOXIDE; CELLULOSE, MICROCRYSTALLINE; HYPROMELLOSE, UNSPECIFIED; TITANIUM DIOXIDE; POLYETHYLENE GLYCOL, UNSPECIFIED; MAGNESIUM STEARATE

Drug Facts

ACTIVE INGREDIENT

Cetirizine HCl 10mg

PURPOSE

Antihistamine

KEEP OUT OF REACH OF CHILDREN

In case of accidental overdose, contact a doctor or Poison Control Center (1-800-222-1222) right away

INDICATIONS AND USAGE

Temporarily relieves these symptoms due to hay fever or other upper respiratory allergies:

runny nose, sneezing, itchy/watery eyes, itching of the nose or throat

WARNINGS

Do not useif you have ever had an allergic reaction to this product or any of its ingredients or an antihistamine containing hydroxyzine

Ask a doctor before useif you have liver or kidney disease. Your doctor should determine if you need a different dose.

Ask a doctor or pharmacist before use if you aretaking sedatives or tranquilizers

When using this productdrowsiness may occur. Avoid alcoholic drinks. Alcohol, sedatives and tranquilizers may increase drowsiness. Be careful when driving a motor vehicle or operating machinery.

Stop use and ask a doctorif an allergic reaction to this product occurs. Seek medical help right away.

DOSAGE AND ADMINISTRATION

Adult and children over 6 years old:One 10mg tablet once daily: no more than one 10mg tablet in 24 hours. A 5mg product may be appropriate for less severe symptoms

Adults 65 years and over:ask a doctor

Children under 6 years of age:ask a doctor

Consumers with liver or kidney disease: ask a doctor

PREGNANCY

If pregnant of breast-feeding:

If breast-feeding: not recommended.

If pregnant: ask a health professional before use.

INACTIVE INGREDIENT

colloidal silicon dioxide, croscarmellose sodium, hypromellose, lactose monohydrate, magnesium stearate, microcrystalline cellulose, polyethylene glycol, titanium dioxide

OTHER SAFETY INFORMATION

Store between 20-25 degrees celcius (68-77 degrees farhenheit).

Do not use if imprinted seal under bottle cap is broken or missing

You may report side effects 1-888-952-0050